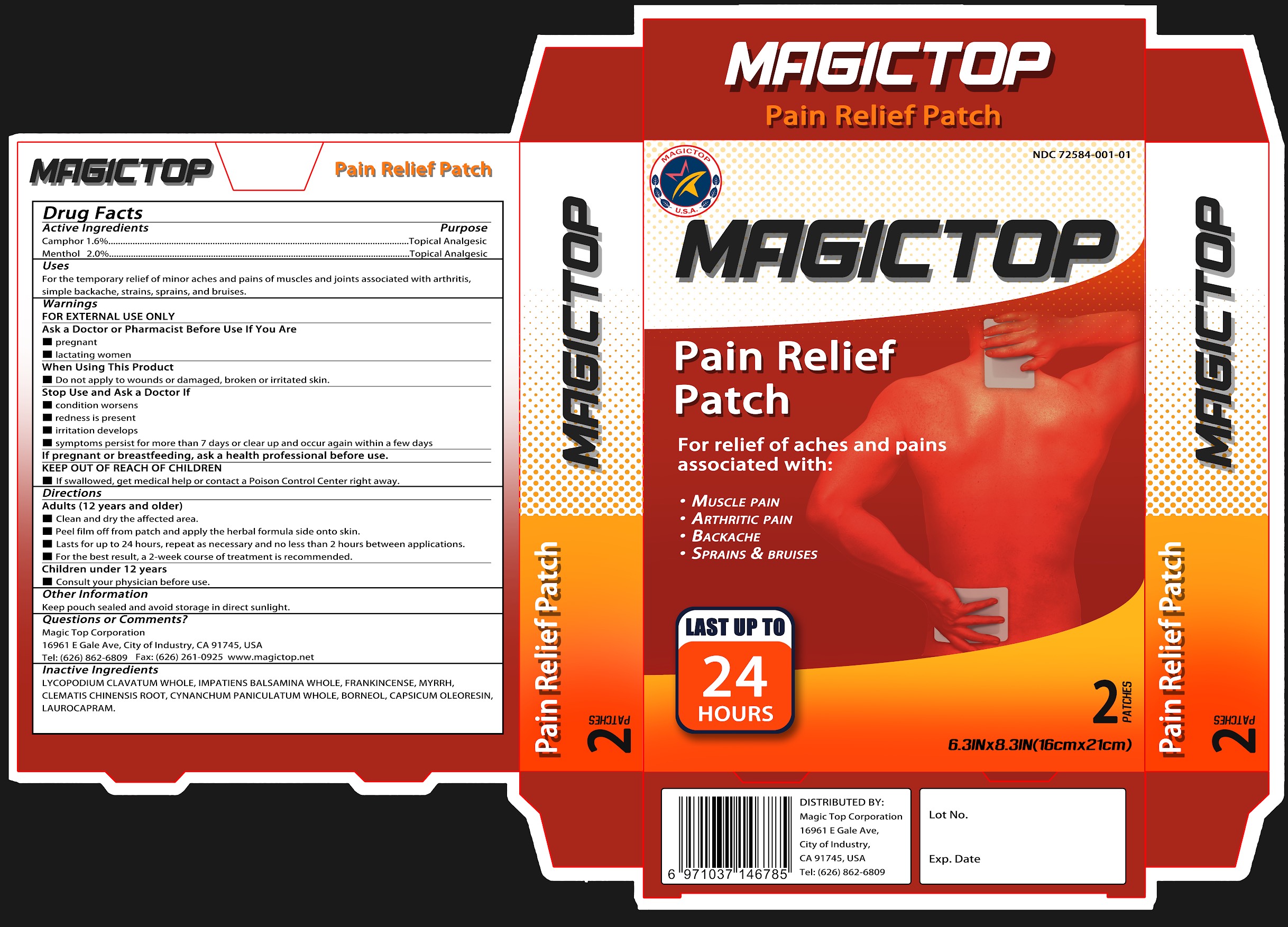 DRUG LABEL: Magictop Pain Relief Patch
NDC: 72584-001 | Form: PATCH
Manufacturer: Zunyi Jici Bio-Health Products Co Ltd
Category: otc | Type: HUMAN OTC DRUG LABEL
Date: 20181228

ACTIVE INGREDIENTS: CAMPHOR (SYNTHETIC) 1.6 g/100 g; MENTHOL 2 g/100 g
INACTIVE INGREDIENTS: LYCOPODIUM CLAVATUM WHOLE; IMPATIENS BALSAMINA WHOLE; FRANKINCENSE; MYRRH; CLEMATIS CHINENSIS ROOT; CYNANCHUM PANICULATUM WHOLE; BORNEOL; CAPSICUM OLEORESIN; LAUROCAPRAM

Zunyi Jici Bio-Health Products Co Ltd

Active Ingredients

Camphor 1.6%
Menthol 2.0%

Purpose

Camphor Topical Analgesic
Menthol Topical Analgesic

Uses

For the temporary relief of minor aches and pains of muscles and joints associated with arthritis, simple backache, strains, sprains, and bruises.

Warnings

FOR EXTERNAL USE ONLY

Ask a Doctor or Pharmacist Before Use If You Are

pregnant.
lactating women.

When Using This Product

Do not apply to wounds or damaged, broken or irritated skin.

Stop Use and Ask a Doctor If

condition worsens.
redness is present.
irritation develops.
symptoms persist for more than 7 days or clear up and occur again within a few days.

KEEP OUT OF REACH OF CHILDREN.

If swallowed, get medical help or contact a Poison Control Center right away.

Directions

Adults (12 years and older)
- Clean and dry the affected area.
- Peel film off from patch and apply the herbal formula side onto skin.
- Lasts for up to 24 hours; repeat as necessary and no less than 2 hours between applications.
- For the best result, a 2-week course of treatment is recommended.
- Children under 12 years: Consult your physician.

Other Information

Keep pouch sealed and avoid storage in direct sunlight.

Questions or Comments?

Magic Top Corp
16961 E Gale Ave, City of Industry, CA91745, USA
Tel: (626) 862-6809 Fax: (626)261-0925 www.magictop.net

Inactive Ingredients

LYCOPODIUM CLAVATUM WHOLE, IMPATIENS BALSAMINA WHOLE， FRANKINCENSE, MYRRH, CLEMATIS CHINENSIS ROOT, CYNANCHUM PANICULATUM WHOLE, BORNEOL, CAPSICUM OLEORESIN, LAUROCAPRAM

Distribted by

Magic Top Corp
16961 E Gale Ave, City of Industry, CA91745, USA
(626) 862-6809